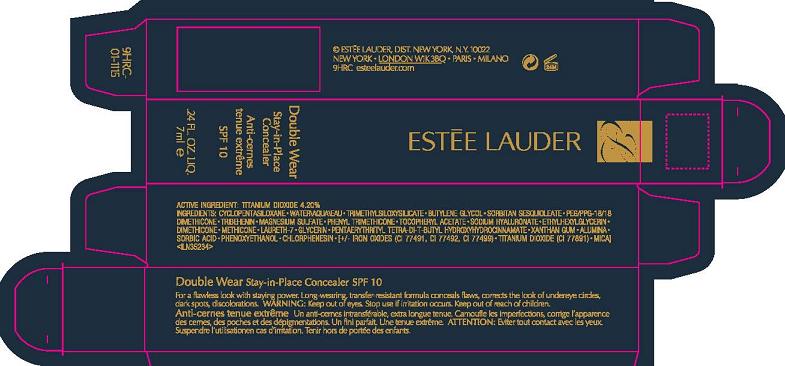 DRUG LABEL: DOUBLE WEAR
NDC: 11559-969 | Form: LIQUID
Manufacturer: ESTEE LAUDER INC
Category: otc | Type: HUMAN OTC DRUG LABEL
Date: 20100513

ACTIVE INGREDIENTS: TITANIUM DIOXIDE 4.2 mL/100 mL

ACTIVE INGREDIENT: TITANIUM DIOXIDE 4.2%

WARNINGS

WARNING: KEEP OUT OF EYES. STOP USE IF IRRITATION OCCURS. KEEP OUT OF REACH OF CHILDREN.

PACKAGE LABEL

PRINCIPAL DISPLAY PANEL:

ESTEE LAUDER

DOUBLE WEAR

STAY-IN-PLACE CONCEALER SPF 10

.24 FL OZ LIQ/ 7 ML

ESTEE LAUDER DIST,
NEW YORK, NY 10022